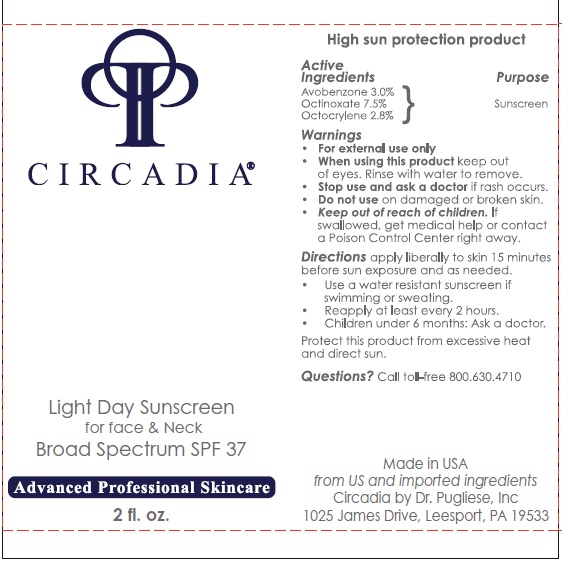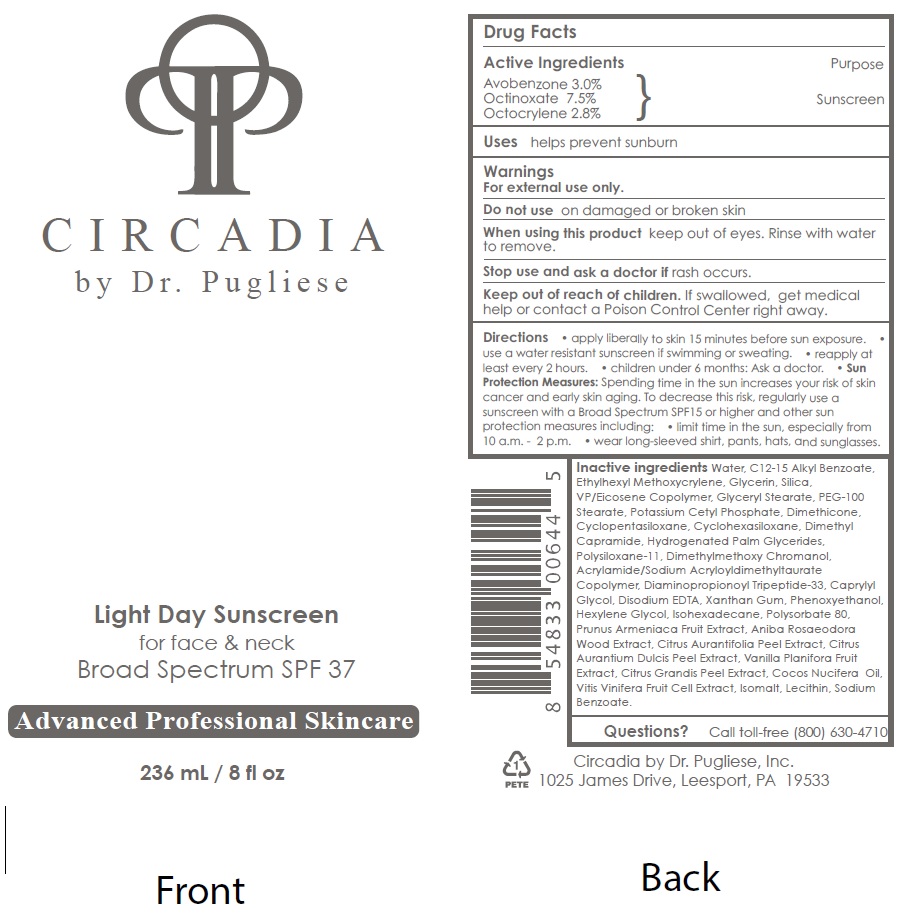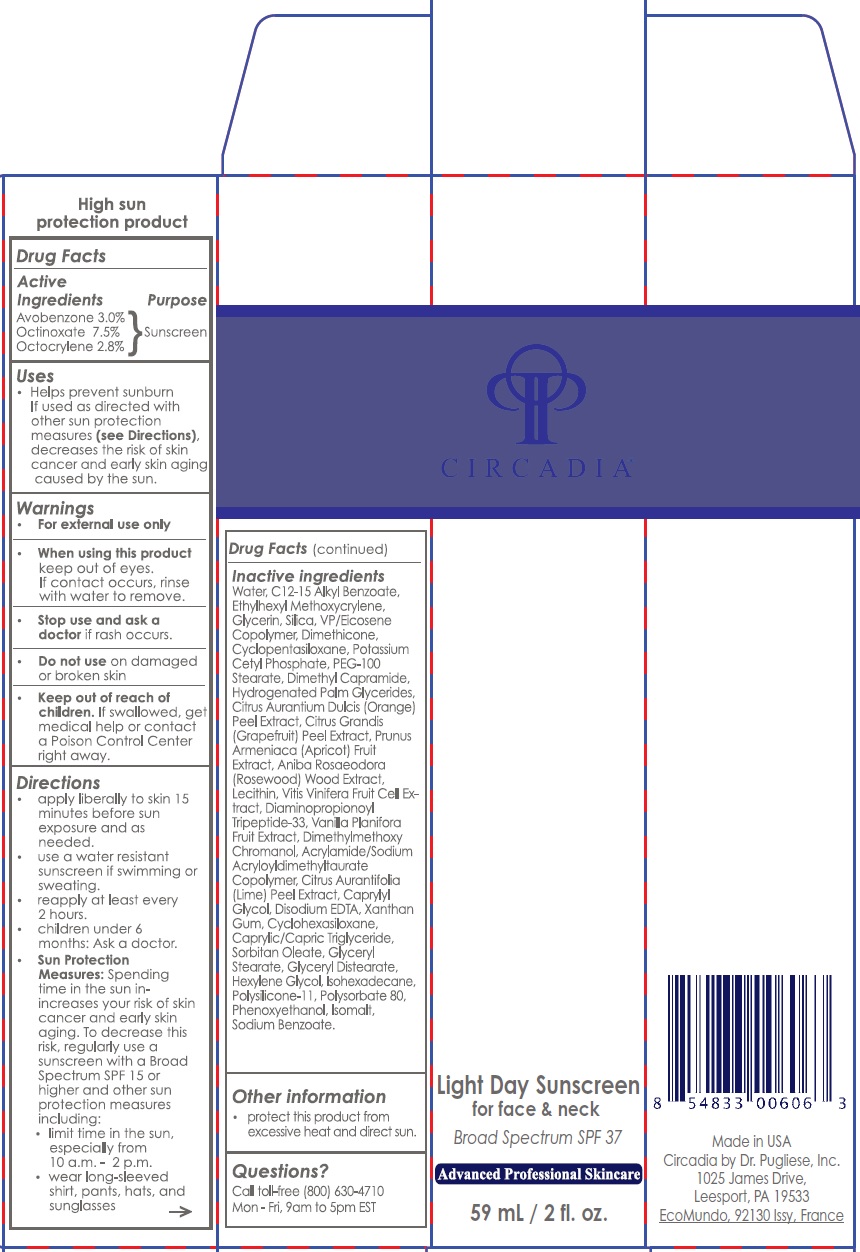 DRUG LABEL: Light Day Sunscreen SPF 37
NDC: 76458-301 | Form: LOTION
Manufacturer: Circadia by Dr Pugliese, Inc.
Category: otc | Type: HUMAN OTC DRUG LABEL
Date: 20231215

ACTIVE INGREDIENTS: AVOBENZONE 30 mg/1 mL; OCTINOXATE 75 mg/1 mL; OCTOCRYLENE 28 mg/1 mL
INACTIVE INGREDIENTS: WATER; ALKYL (C12-15) BENZOATE; ETHYLHEXYL METHOXYCRYLENE; GLYCERIN; SILICON DIOXIDE; GLYCERYL MONOSTEARATE; PEG-100 STEARATE; POTASSIUM CETYL PHOSPHATE; DIMETHICONE; CYCLOMETHICONE 5; CYCLOMETHICONE 6; DIMETHYL CAPRAMIDE; HYDROGENATED PALM GLYCERIDES; DIMETHYLMETHOXY CHROMANOL; CAPRYLYL GLYCOL; EDETATE DISODIUM ANHYDROUS; XANTHAN GUM; PHENOXYETHANOL; HEXYLENE GLYCOL; ISOHEXADECANE; POLYSORBATE 80; ANIBA ROSAEODORA WOOD; LIME PEEL; ORANGE PEEL; VANILLA BEAN; CITRUS MAXIMA FRUIT RIND; ISOMALT; SODIUM BENZOATE

Light Day Sunscreen SPF 37

Active Ingredients

Avobenzone 3.0%
Octinoxate 7.5%
Octocrylene 2.8%

Purpose

Sunscreen

Uses

helps prevent sunburn

Warnings

For external use only.

Do not use

on damaged or broken skin

When using this product

keep out of eyes. Rinse with water to remove.

Stop use and ask a doctor if

rash occurs.

Keep out of reach of children.

If swallowed, get medical help or contact a Poison Control Center right away.

Directions

• apply liberally to skin 15 minutes before sun exposure. • use a water resistant sunscreen if swimming or sweating. • reapply at least every 2 hours. • children under 6 months: Ask a doctor. • Sun Protection Measures: Spending time in the sun increases your risk of skin cancer and early skin aging. To decrease this risk, regularly use a sunscreen with a Broad Spectrum SPF15 or higher and other sun protection measures including: • limit time in the sun, especially from 10 a.m. - 2 p.m. • wear long-sleeved shirt, pants, hats, a nd sunglasses.

Inactive ingredients

Water, C12-15 Alkyl Benzoate, Ethylhexyl Methoxycrylene, Glycerin, Silica, VP/Eicosene Copolymer, Glyceryl Stearate, PEG-100 Stearate, Potassium Cetyl Phosphate, Dimethicone, Cyclopentasiloxane, Cyclohexasiloxane, Dimethyl Capramide, Hydrogenated Palm Glycerides, Polysiloxane-11, Dimethylmethoxy Chromanol, Acrylamide/Sodium Acryloyldimethyltaurate Copolymer, Diaminopropionoyl Tripeptide-33, Caprylyl Glycol, Disodium EDTA, Xanthan Gum, Phenoxyethanol, Hexylene Glycol, Isohexadecane, Polysorbate 80, Prunus Armeniaca Fruit Extract, Aniba Rosaeodora Wood Extract, Citrus Aurantifolia Peel Extract, Citrus Aurantium Dulcis Peel Extract, Vanilla Planifora Fruit Extract, Citrus Grandis Peel Extract, Cocos Nucifera Oil, Vitis Vinifera Fruit Cell Extract, Isomalt, Lecithin, Sodium Benzoate.

Questions?

Call toll-free (800) 630-4710